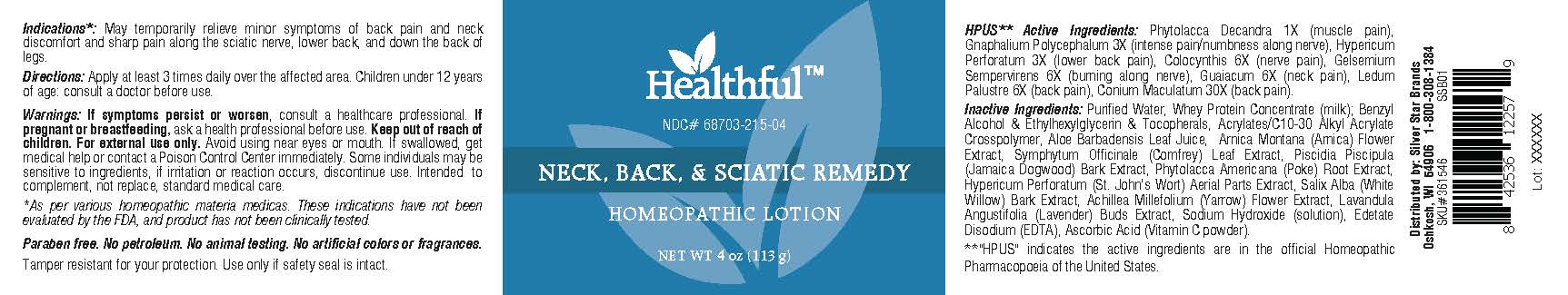 DRUG LABEL: Neck Back Sciatic Remedy
NDC: 68703-215 | Form: LOTION
Manufacturer: Silver Star Brands
Category: homeopathic | Type: HUMAN OTC DRUG LABEL
Date: 20230304

ACTIVE INGREDIENTS: PHYTOLACCA AMERICANA ROOT 1 [hp_X]/113 g; PSEUDOGNAPHALIUM OBTUSIFOLIUM 3 [hp_X]/113 g; HYPERICUM PERFORATUM 3 [hp_X]/113 g; CONIUM MACULATUM FLOWERING TOP 30 [hp_X]/113 g; GELSEMIUM SEMPERVIRENS ROOT 6 [hp_X]/113 g; CITRULLUS COLOCYNTHIS FRUIT 6 [hp_X]/113 g; GUAIACUM OFFICINALE RESIN 6 [hp_X]/113 g; LEDUM PALUSTRE TWIG 6 [hp_X]/113 g
INACTIVE INGREDIENTS: PISCIDIA PISCIPULA WHOLE; PHYTOLACCA AMERICANA FRUIT; ALOE VERA LEAF; ARNICA MONTANA FLOWER; COMFREY LEAF; ACHILLEA MILLEFOLIUM FLOWER; HYPERICUM PERFORATUM FLOWER; WHEY; WATER; SALIX ALBA BARK; EDETATE DISODIUM; BENZYL ALCOHOL; ETHYLHEXYLGLYCERIN; CARBOMER INTERPOLYMER TYPE A (ALLYL SUCROSE CROSSLINKED); SODIUM HYDROXIDE; ASCORBIC ACID; ALPHA-TOCOPHEROL; LAVANDULA ANGUSTIFOLIA FLOWER

Healthful™ Neck, Back & Sciatic Remedy

HPUS** Active Ingredients: Phytolacca Decandra 1X (muscle pain), Gnaphalium Polycephalum 3X (intense pain/numbness along nerve), Hypericum Perforatum 3X (lower back pain), Colocynthis 6X (nerve pain), Gelsemium Sempervirens 6X (burning along nerve), Guaiacum 6X (neck pain), Ledum Palustre 6X (back pain), Conium Maculatum 30X (back pain).

**"HPUS" indicates the active ingredients are in the official Homeopathic Pharmacopoeia of the United States.

Uses*

Indications*: May temporarily relieve minor symptoms of back pain and neck discomfort and sharp pain along the sciatic nerve, lower back, and down the back of legs.

*As per various homeopathic materia medicas. These indications have not been evaluated by the FDA, and product has not been clinically tested.

Warnings

Warnings: If symptoms persist or worsen, consult a healthcare professional. If pregnant or breastfeeding, ask a health professional before use. Keep out of reach of children. For external use only. Avoid using near eyes or mouth. If swallowed, get medical help or contact a Poison Control Center immediately. Some individuals may be sensitive to ingredients, if irritation or reaction occurs, discontinue use. Intended to complement, not replace, standard medical care.

Directions

Directions: Apply at least 3 times daily over the affected area. Children under 12 years of age: consult a doctor before use.

OTHER SAFETY INFORMATION

Paraben free. No petroleum. No animal testing. No artivicial colors or fragrances.

Tamper resistant for your protection. Use only if safety seal is intact.

Inactive Ingredients

Purified Water, Whey Protein Concentrate (milk); Benzyl Alcohol & Ethylhexylglycerin & Tocopherals, Acrylates/C10-30 Alkyl Acrylate Crosspolymer, Aloe Barbadensis Leaf Juice, Arnica Montana (Arnica) Flower Extract, Symphytum Officinale (Comfrey) Leaf Extract, Piscidia Piscipula (Jamaica Dogwood) Bark Extract, Phytolacca Americana (Poke) Root Extract, Hypericum Perforatum (St. John's Wort) Aerial Parts Extract, Salix Alba (White Willow) Bark Extract, Achillea Millefolium (Yarrow) Flower Extract, Lavandula Angustifolia (Lanvender) Buds Extract, Sodium Hydroxide (solution), Edetate Disodium (EDTA), Ascorbic Acid (Vitamin C powder).

PREGNANCY OR BREAST FEEDING

If pregnant or breastfeeding, ask a health professional before use.

PURPOSE

Homeopathic Lotion